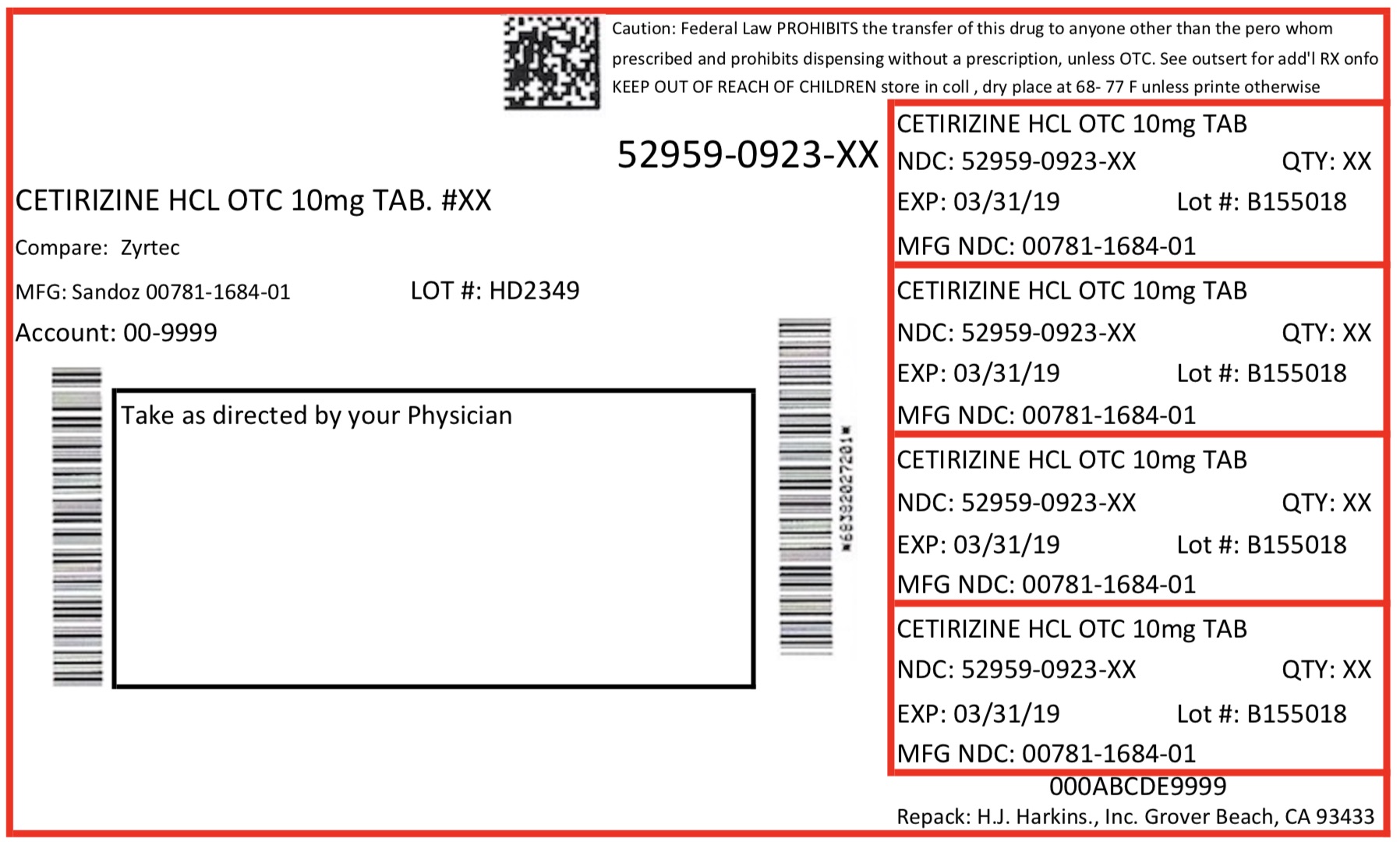 DRUG LABEL: CETIRIZINE HYDROCHLORIDE
NDC: 52959-923 | Form: TABLET
Manufacturer: H. J. Harkins Company Inc.
Category: prescription | Type: HUMAN PRESCRIPTION DRUG LABEL
Date: 20171201

ACTIVE INGREDIENTS: CETIRIZINE HYDROCHLORIDE 10 mg/1 1

Active Ingredient

(in each tablet)

Cetirizine HCl 10 mg

Purpose

Antihistamine

Keep out of Reach of Children

In case of overdose, get medical help or contact a Poison Control Center right away.

USES

Temporarily relieves these symptoms due to hay fever or other upper respiratory allergies:

•
runny nose
•
sneezing
•
itchy, watery eyes
•
itching of the nose or throat

Warnings

antihistamine containing hydroxyzine.

Ask a doctor before use if you have liver or kidney disease. Your doctor should determine if you need a different dose.

Ask a doctor or pharmacist before use if you are taking tranquilizers or sedatives.

When using this product

•
drowsiness may occur
•
avoid alcoholic drinks
•
alcohol, sedatives, and tranquilizers may increase drowsiness
•
be careful when driving a motor vehicle or operating machinery

Stop use and ask a doctor if an allergic reaction to this product occurs. Seek medical help right away.

If pregnant or breast-feeding:

•
if breast-feeding: not recommended
•
if pregnant: ask a health professional before use.

Keep out of reach of children. In case of overdose, get medical help or contact a Poison Control Center right away.

Directions

dults and children 6 years and over

One 10 mg tablet once daily; do not take more than one 10 mg tablet in 24 hours. A 5 mg product may be appropriate for less severe symptoms.

adults 65 years and over

ask a doctor

children under 6 years of age

ask a doctor

consumers with liver or kidney disease

ask a doctor

Inactive Ingredient

Corn starch, hypromellose, lactose monohydrate, macrogol, magnesium stearate, povidone and titanium dioxide.

Questions? 1-800-525-8747

Manufactured in India by Sandoz Private Ltd.,

for Sandoz Inc., Princeton, NJ 08540

Rev.06/2013